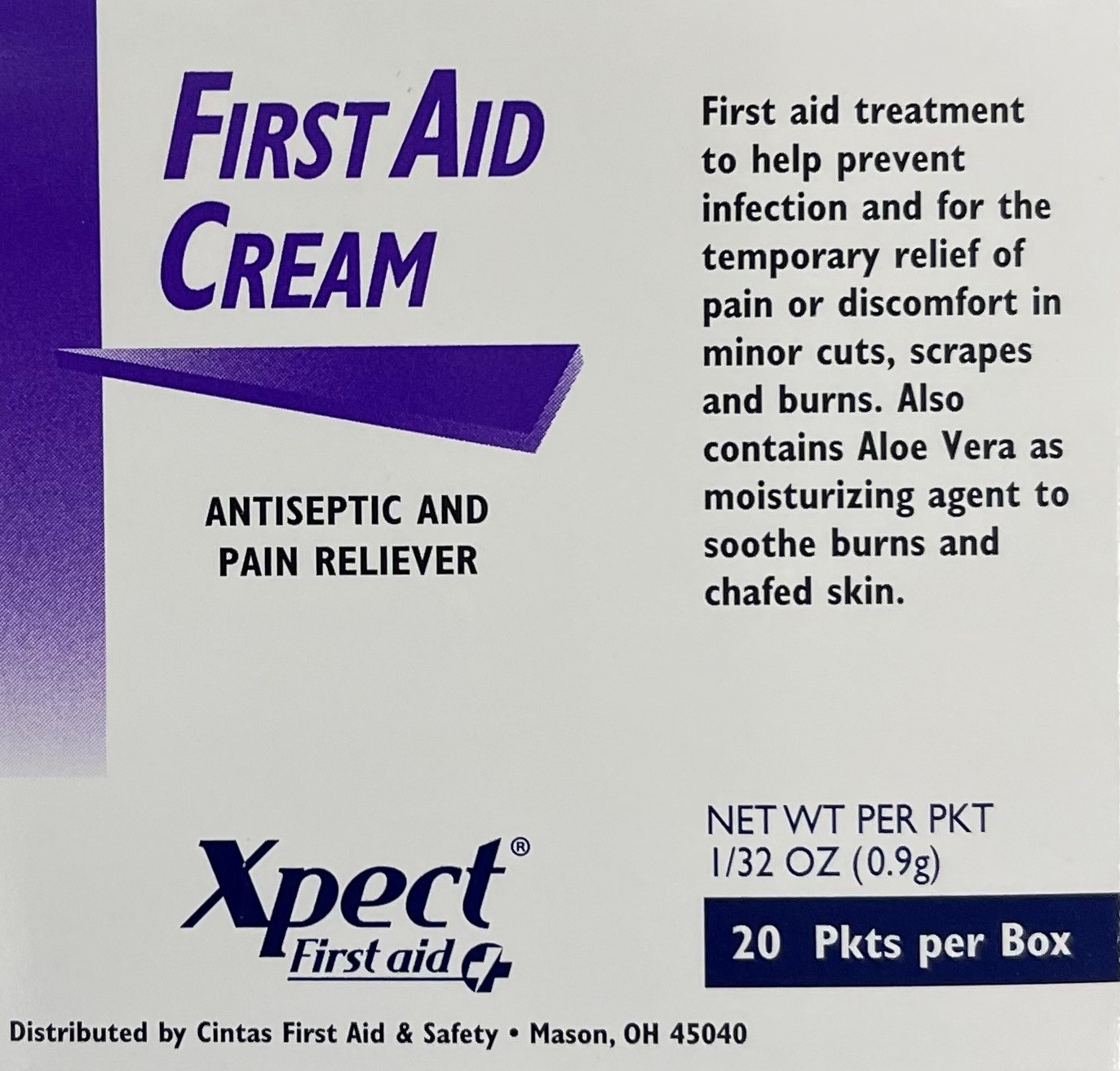 DRUG LABEL: Xpect First Aid Cream
NDC: 82940-214 | Form: CREAM
Manufacturer: Shares Inc
Category: otc | Type: HUMAN OTC DRUG LABEL
Date: 20220819

ACTIVE INGREDIENTS: BENZALKONIUM CHLORIDE 0.13 g/100 g; LIDOCAINE HYDROCHLORIDE 0.5 g/100 g
INACTIVE INGREDIENTS: ALOE VERA LEAF; EDETATE DISODIUM; GLYCERIN; GLYCERYL MONOSTEARATE; MINERAL OIL; POLYETHYLENE GLYCOL, UNSPECIFIED; PROPYLENE GLYCOL; PROPYLPARABEN; WATER; STEARIC ACID; CETYL ALCOHOL; DIAZOLIDINYL UREA; METHYLPARABEN; TROLAMINE

xpect first aid cream

Active Ingredients

Benzalkonium chloride 0.13%

Lidocaine HCL 0.5%

Purpose

First aid antiseptic

External analgesic

Uses

first aid to help prevent infection and for the temporary relief of pain in minor cuts, scrapes and burns

Warnings

For external use only

Do not use

- in the eyes or apply over large areas of the body
- longer than 1 week unless directed by a doctor
- in large quantitites, particularly over raw surfaces or blistered areas

Ask a doctor before use if you have

- deep or puncture wounds
- animal bites
- serious burns

Stop use and ask a doctor if

condition persists or gets worse

- symptoms persist for more than 7 days
- condition clears up and occurs again within a few days
- a rash or other allergic reaction develops

Keep out of reach of children

If swallowed, get medical help or contact a Poison Control Center right away.

Directions

adults and children 2 years of age and older

- clean the affected area
- may be covered with a sterile bandage
- apply a small amount (an amount equal to the surface area of the tip of finger) 1 to 3 times daily

Other information

- do not use if packet is torn, cut or opened
- store at room temperature (do not freeze)
- see packet for Lot Number and expiration date

Inactive ingredients

aloe vera, cetyl alcohol, diazolidinyl urea, edetate disodium, glycerin, glyceryl monosterate, methylparaben, mineral oil, polyethylene glycol, propylene glycol, propylparaben, purified water, stearic acid, trolamine

Questions

1-877-973-2811

PACKAGE LABEL

First Aid Cream

Antixeptic and pain reliever

Net Wt per Pkt 1.32 oz (0.9 g)

20 pkts per box